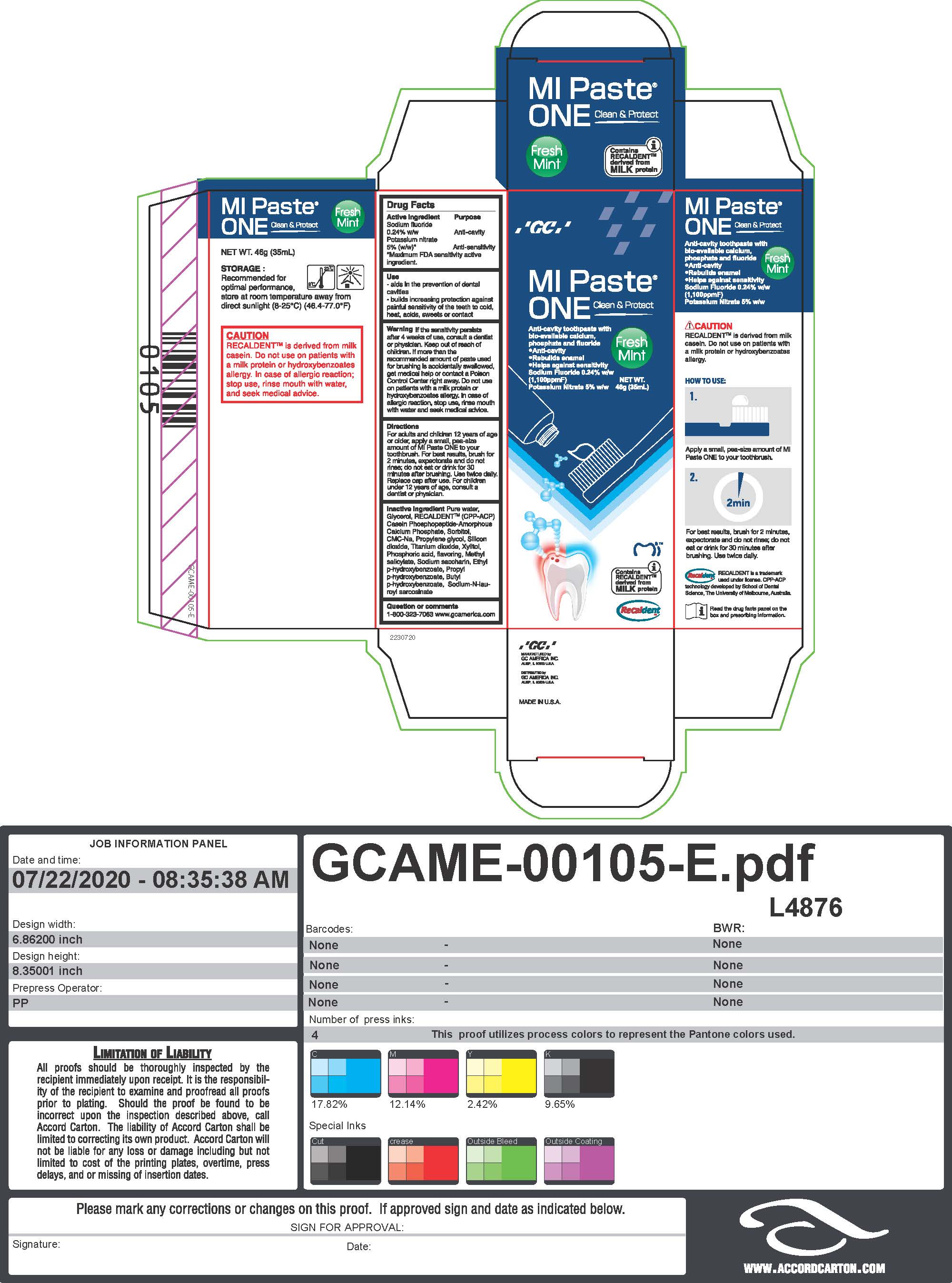 DRUG LABEL: MIPaste One
NDC: 61596-400 | Form: PASTE, DENTIFRICE
Manufacturer: GC America Inc.
Category: otc | Type: HUMAN OTC DRUG LABEL
Date: 20251219

ACTIVE INGREDIENTS: POTASSIUM NITRATE 5 g/100 g; SODIUM FLUORIDE 0.24 g/100 g
INACTIVE INGREDIENTS: CALCIUM PHOSPHATE, UNSPECIFIED FORM; TITANIUM DIOXIDE; METHYL SALICYLATE; ETHYLPARABEN; WATER; SORBITOL; CARBOXYMETHYLCELLULOSE SODIUM, UNSPECIFIED FORM; PROPYLENE GLYCOL; PROPYLPARABEN; SACCHARIN SODIUM; XYLITOL; SILICON DIOXIDE; GLYCERIN; PHOSPHORIC ACID; BUTYLPARABEN; SODIUM LAUROYL SARCOSINATE

MIPaste One

ACTIVE INGREDIENT

Sodium fluoride

0.24% w/w

Potassium nitrate

5% (w/w)

INDICATIONS AND USAGE

- aids in prevention of dental cavities

- builds increasing protection against painful sensitivity of the teeth to cold, heat, acids, sweets or contact

WARNINGS

Warning If the sensitivity persists after 4 weeks of use, consult a dentist or physician. Keep out of reach of children. If more than the recommended amount of paste used for brushing is accidentally swallowed, get medical help or contact a Poison Control Center right away. Do not use on patients with a milk protein or hydroxybenzoates allergy. In case of allergic reaction, stop use, rinse mouth with water and seek medical advice.

DOSAGE AND ADMINISTRATION

For adults and children 12 years of age or older, apply a small, pea-size amount of MI Paste One to your toothbrush. For best results, brush for 2 minutes, expectorate and do not rinse; do not eat or drink for 30 minutes after brushing. Use twice daily. Replace cap after use. For children under 12 years of age, consult a dentist or physician.

Inactive ingredient Pure water, Glycerol, RECALDENT (CPP-ACP), Casein Phosphopeptide-Amorphous, Calcium Phosphate, Sorbitol, CMC-NA, Propylene glycol, Silicon dioxide, Titanium dioxide, Xylitol, Phosphoric acid, flavoring, Methyl salicylate, Sodium saccharin, Ethyl p-hydroxybenzoate, Propyl p-hydroxybenzoate, Butyl p-hydroxybenzoate, Sodium-N-lauroyl sarcosinate

Warning Keep out of reach of children.

PURPOSE

Anti-cavity

Anti-sensitivity